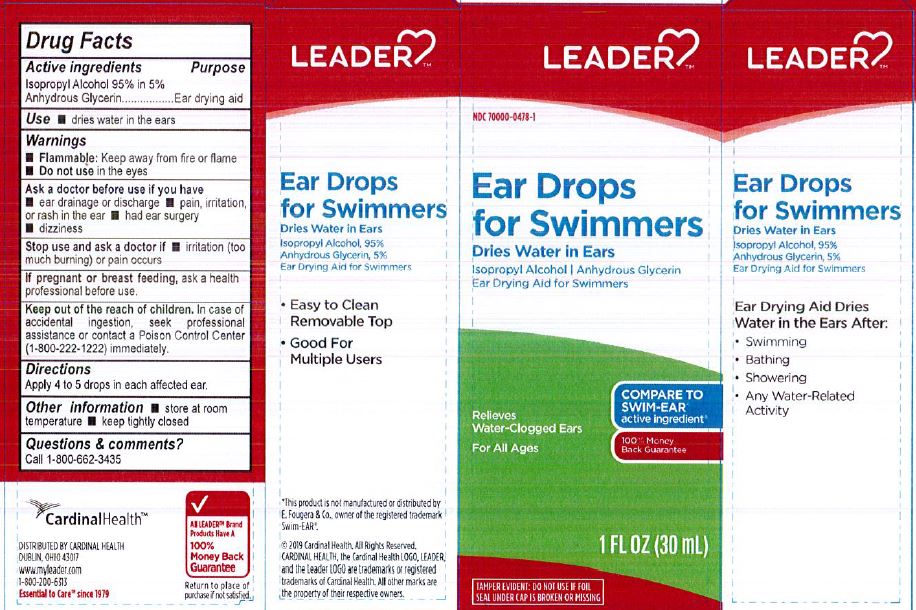 DRUG LABEL: LEADER Ear Drops for Swimmers
NDC: 70000-0478 | Form: LIQUID
Manufacturer: Cardinal Health, 110 dba Leader
Category: otc | Type: HUMAN OTC DRUG LABEL
Date: 20231222

ACTIVE INGREDIENTS: ISOPROPYL ALCOHOL 950 mg/1 mL
INACTIVE INGREDIENTS: GLYCERIN

LEADER Ear Drops for Swimmers

ACTIVE INGREDIENT

Isopropyl Alcohol 95% in 5% Anhydrous Glycerin

PURPOSE

Ear Drying Aid

INDICATIONS AND USAGE

Dries water in the ears

WARNINGS

Flammable: Keep away from fire or flame

Do not use in the eyes

DOSAGE AND ADMINISTRATION

Apply 4 to 5 drops in each affected ear

WHEN USING

Store at room temperature

keep tightly closed

INACTIVE INGREDIENT

Glycerin

Keep out of reach of children. in case of accidental ingestion, seek professional assitance or contact a poison control center immediately. (1-800-222-1222)